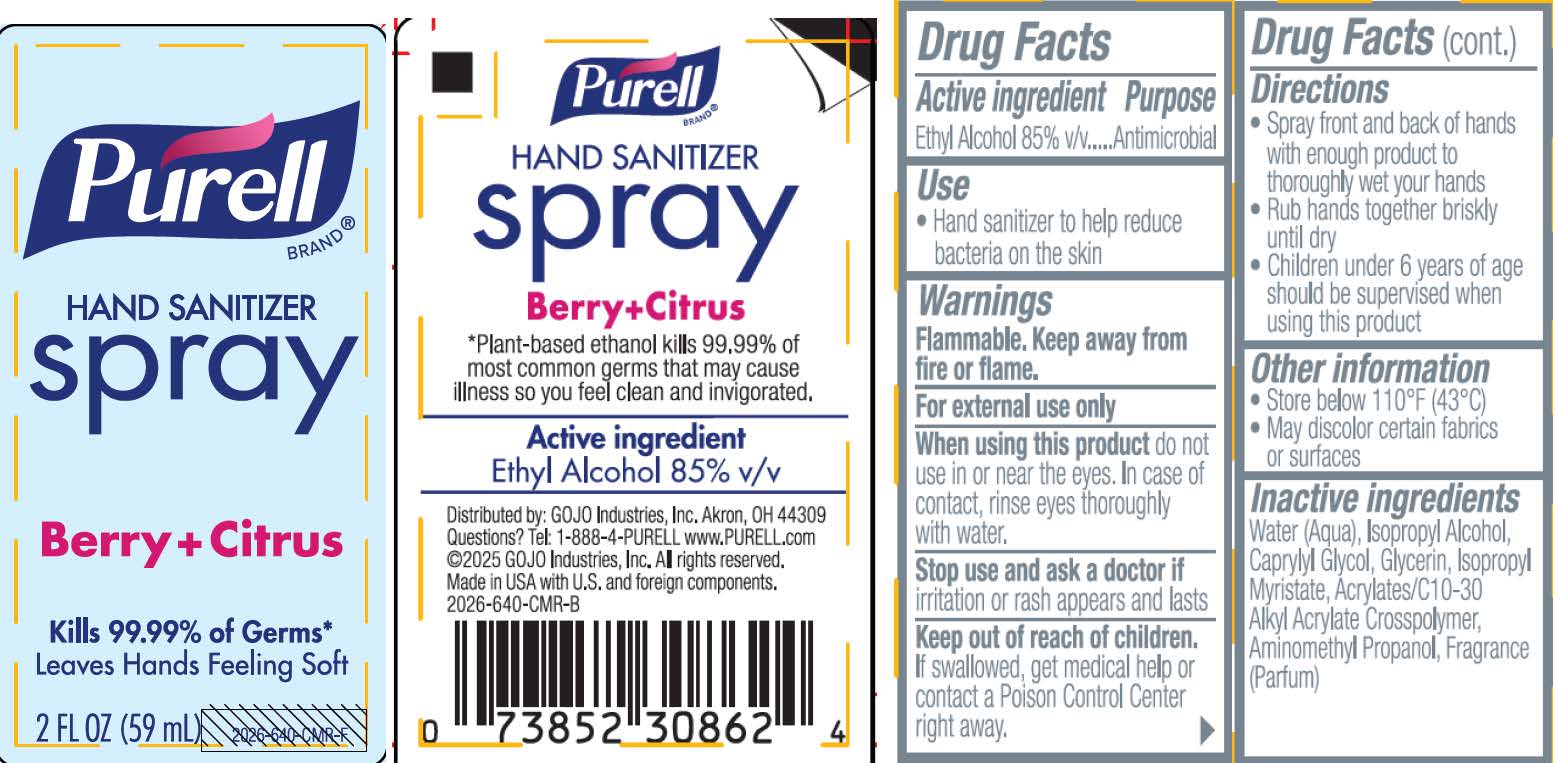 DRUG LABEL: PURELL Hand Sanitizer SP Berry and Citrus
NDC: 21749-909 | Form: SPRAY
Manufacturer: GOJO Industries, Inc.
Category: otc | Type: HUMAN OTC DRUG LABEL
Date: 20250926

ACTIVE INGREDIENTS: ALCOHOL 85 mL/100 mL
INACTIVE INGREDIENTS: WATER; ISOPROPYL ALCOHOL; CAPRYLYL GLYCOL; GLYCERIN; ISOPROPYL MYRISTATE; ACRYLATES/C10-30 ALKYL ACRYLATE CROSSPOLYMER (60000 MPA.S); AMINOMETHYLPROPANOL

PURELL® Hand Sanitizer Spray Berry and Citrus

Active ingredient

Ethyl alcohol 85% v/v

Purpose

Antimicrobial

Use

Hand sanitizer to help reduce bacteria on the skin

Warnings

Flammable. Keep away from fire or flame.

For external use only

When using this product do not use in or near the eyes. In case of contact, rinse eyes thoroughly with water.

Stop use and ask a doctor if irritation or rash appears and lasts

Keep out of reach of children.If swallowed, get medical help or contact a Poison Control Center right away.

Directions

· Spray front and back of hands with enough product to thoroughly wet your hands

· Rub hands together briskly until dry

· Children under 6 years of age should be supervised when using this product.

Inactive ingredients

Water (Aqua), Isopropyl Alcohol, Caprylyl Glycol, Glycerin, Isopropyl Myristate, Acrylates/C10-30 Alkyl Acrylate Crosspolymer, Aminomethyl Propanol, Fragrance (Parfum)